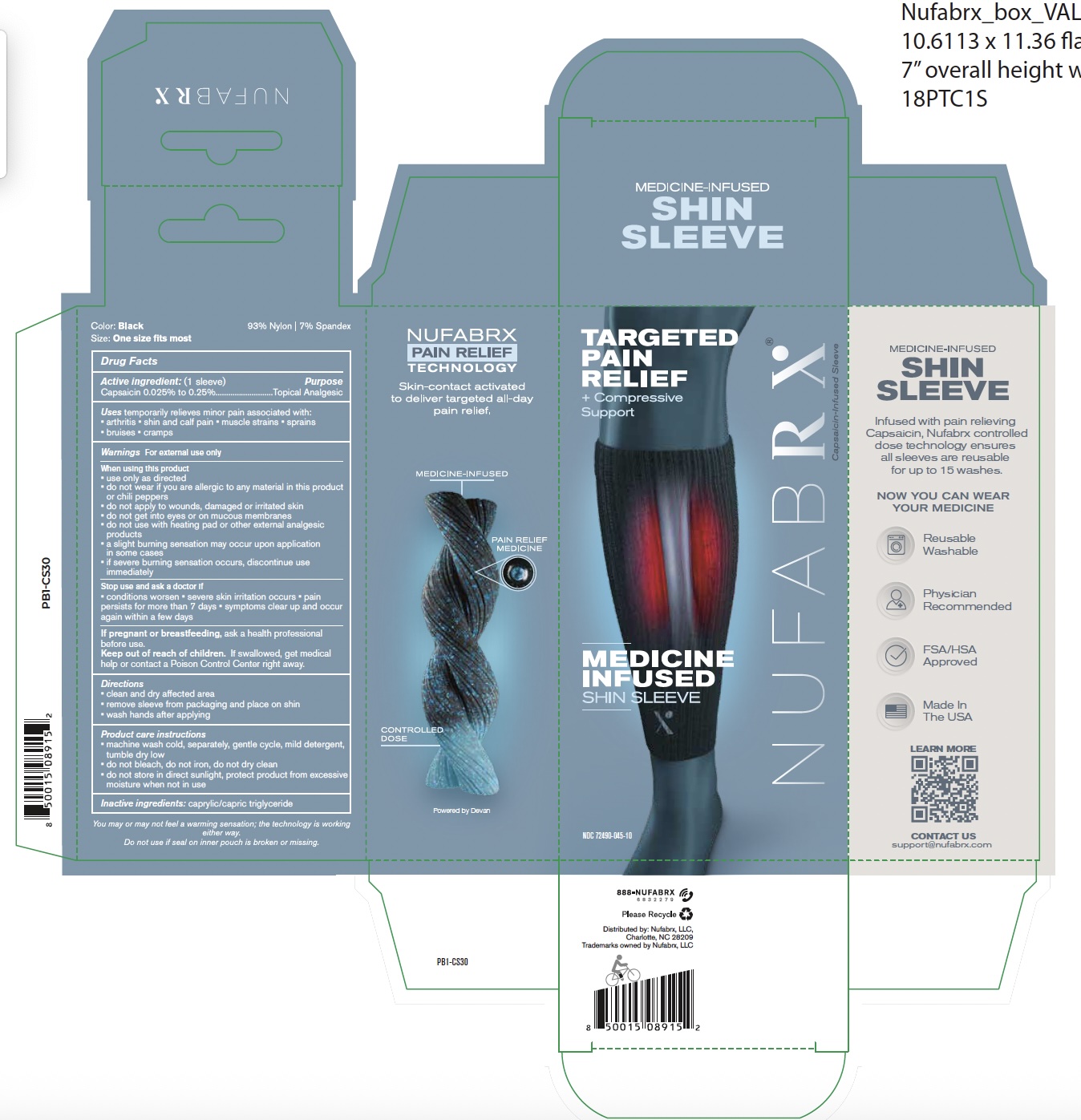 DRUG LABEL: Nufabrx Shin Sleeve
NDC: 72490-045 | Form: CLOTH
Manufacturer: Nufabrx LLC
Category: otc | Type: HUMAN OTC DRUG LABEL
Date: 20251230

ACTIVE INGREDIENTS: CAPSAICIN 0.25 g/100 g
INACTIVE INGREDIENTS: CAPRYLIC/CAPRIC/LINOLEIC TRIGLYCERIDE

72490-045 Nufabrx Medicine Infused Shin Sleeve

Active Ingredient

Capsaicin 0.25%

Purpose

Topical Analgesic

Uses

Temporary relieves of minor pain associated with: arthritis, shin and calf pain, muscle strains, sprains, bruises and cramps.

Warnings

For external use only

When using this product

- use only as directed
- do not wear if you are allergic to any material in this product or chili peppers
- do not apply to wounds, damaged or irritated skin
- do not get into eyes or on mucous membranes
- do not use with heating pad or other external analgesic products
- a slight burning sensation may occur upon application in some cases
- if severe burning sensation occurs, discontinue use immediately

Stop use and ask doctor if

- Condition worsens
- severe skin irritation occurs
- pain persists more than 7 days
- symptoms clear up and occur again within a few days

If pregnant or beastfeeding

ask a health professional before use.

Keep out of reach of children

If swallowed, get medical help or contact a Poison Control Center right away.

Directions

- Clean and dry affected area
- Remove sleeve from packaging and place on shin
- Wash hands after applying

Product Care instructions

- machine wash cold, separately, gentle cycle, mild detergent, tumble dry low
- do not bleach, do not iron, do not dry clean
- do not store in direct sunlight, protect product from excessive moisture when not in use

Inactive ingredients

caprylic/capric triglyceride